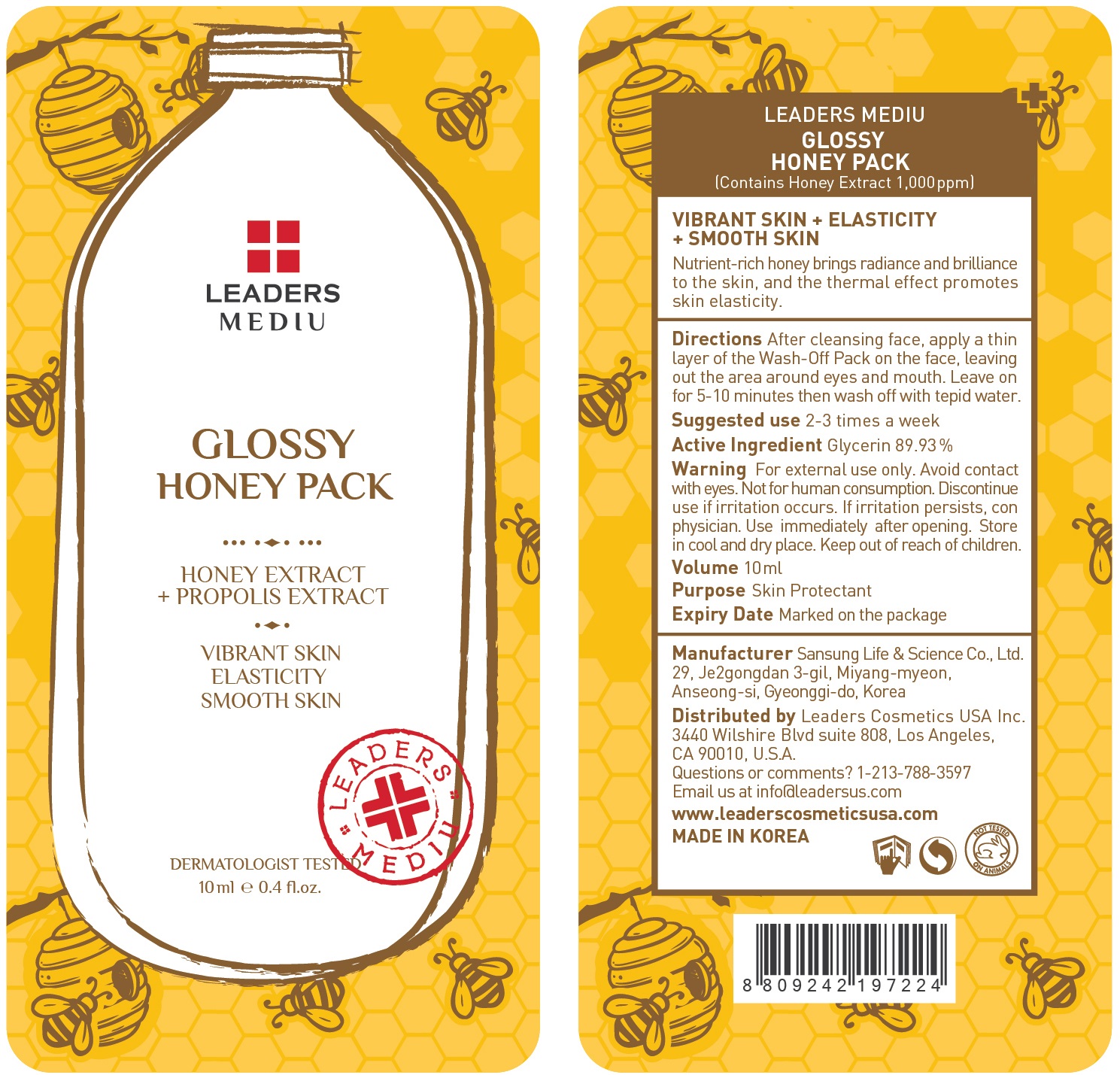 DRUG LABEL: Leaders Mediu Glossy Honey Pack
NDC: 69424-500 | Form: GEL
Manufacturer: SANSUNG LIFE & SCIENCE CO., LTD.
Category: otc | Type: HUMAN OTC DRUG LABEL
Date: 20160201

ACTIVE INGREDIENTS: Glycerin 8.99 g/10 mL
INACTIVE INGREDIENTS: Butylene Glycol; 1,2-Hexanediol

ACTIVE INGREDIENT

Active Ingredient: Glycerin 89.93%

INACTIVE INGREDIENT

Inactive Ingredients: Butylene Glycol, 1,2-Hexanediol, Glycereth-26 , Hydrogenated Poly(C6-14 Olefin), Water, Glyceryl Stearate, PEG-100 Stearate, Hydroxyethyl Acrylate/Sodium Acryloyldimethyl Taurate Copolymer, Squalane, PEG-60 Hydrogenated Castor Oil, Honey Extract, Propolis Extract, Octyldodecanol, Buteth-3, Fragrance, Sodium Benzotriazolyl Butylphenol Sulfonate, Olea europaea (Olive) fruit oil, Tributyl Citrate, BHT, CI 15985, CI 19140

PURPOSE

Purpose: Skin Protectant

WARNINGS

Warnings: For external use only. Avoid contact with eyes. Not for human consumption. Discontinue use if irritation occurs. If irritation persists, consult a physician.

Use immediately after opening. Store in cool and dry place. Keep out of reach of children.

KEEP OUT OF REACH OF CHILDREN

Directions

Directions: After cleansing face, apply a thin layer of the Wash-Off Pack on the face, leaving out the area around eyes and mouth. Leave on for 5-10 minutes then wash off with tepid water. *Suggested use is 2-3 times a week

Directions

Directions: After cleansing face, apply a thin layer of the Wash-Off Pack on the face, leaving out the area around eyes and mouth. Leave on for 5-10 minutes then wash off with tepid water. *Suggested use is 2-3 times a week